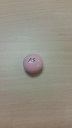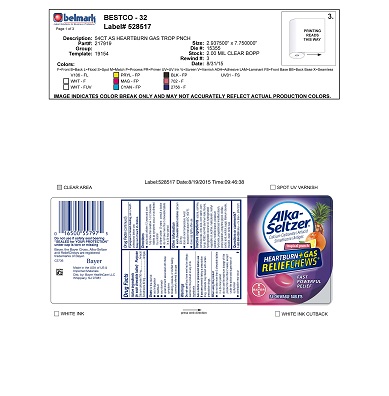 DRUG LABEL: Tropical Panned
NDC: 52642-230 | Form: TABLET, CHEWABLE
Manufacturer: BestCo Inc.
Category: otc | Type: HUMAN OTC DRUG LABEL
Date: 20160215

ACTIVE INGREDIENTS: CALCIUM CARBONATE 750 mg/1 1; DIMETHICONE 80 mg/1 1
INACTIVE INGREDIENTS: CARNAUBA WAX

Calcium Carbonate 750mg
Simethicone 80mg

Active Ingredients

(in each chewable tablet)

Calcium Carbonate 750mg

Simethicone 80mg

Purpose

Antacid

Antigas

INDICATIONS AND USAGE

Uses for the relief of:

- acid indigestion
- heartburn
- sour stomach
- upset stomach associated with these symptoms
- bloating, pressure, or stuffed feeling commonly referred to as gas

Warnings

Do not use if you have ever had an allergic reaction to this product or any of its ingredients

Ask a doctor or pharmacist before use if you are presently taking a prescription drug. Antacids may interact with certain prescription drugs.

When using this product

- do not take more than 5 chewable tablets in a 24-hour period
- do not use the maximum dosage of this product for more than 2 weeks, except under the advice and supervision of a physician
- constipation may occur

PREGNANCY OR BREAST FEEDING

If pregnant or breast-feeding, ask a health professional before use.

Keep out of reach of children

Directions

- adults and children 12 years and over: fully chew then swallow 1 or 2 chewable tablets as symptoms occur, or as directed by a doctor
- children under 12 years : consult a doctor
- do not take more than 5 chewable tablets in a 24-hour period

Other information

- each chewable tablet contains: calcium 330mg
- store at room temperature. Avoid excessive heat above 40C (104F).
- close cap tightly after use

Inactive Ingredients

acacia, carmine, carnauba wax, citric acid, corn starch, corn syrup, FD&C red #40 aluminum lake, flavors, hydrogenated coconut oil, hydrogenated vegetable oil, lecithin, maltodextrin, methly paraben, modified starch, potassium hydroxide, pregelatinized modified starch, propyl paraben, propylene glyclol, shellac, sorbic acid, sorbitol, sugar, titanium dioxide, triacetin, water, white wax

Questions or Comments?

1-800-986-0369 (Mon-Fri 9am-5pm EST)